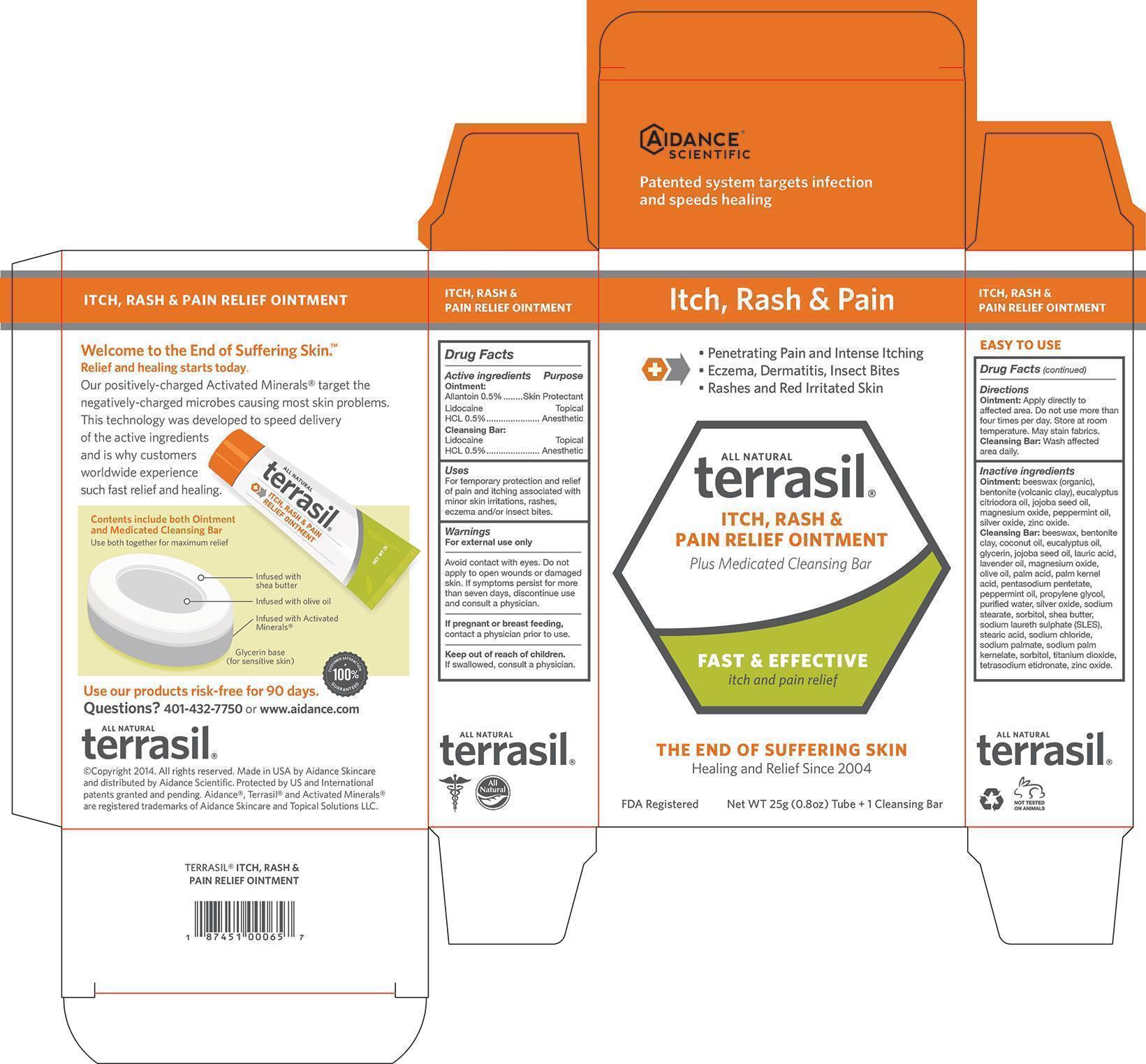 DRUG LABEL: Terrasil Itch, Rash and Pain Relief
NDC: 24909-163 | Form: KIT | Route: TOPICAL
Manufacturer: Aidance Skincare & Topical Solutions, LLC
Category: otc | Type: HUMAN OTC DRUG LABEL
Date: 20140418

ACTIVE INGREDIENTS: ALLANTOIN 0.5 g/100 g; LIDOCAINE HYDROCHLORIDE 0.5 g/100 g; LIDOCAINE HYDROCHLORIDE 0.5 g/100 g
INACTIVE INGREDIENTS: BENTONITE; EUCALYPTUS OIL; JOJOBA OIL; MAGNESIUM OXIDE; PEPPERMINT OIL; SILVER OXIDE; WHITE WAX; ZINC OXIDE; BENTONITE; COCONUT OIL; EUCALYPTUS OIL; GLYCERIN; JOJOBA OIL; LAURIC ACID; LAVENDER OIL; MAGNESIUM OXIDE; OLIVE OIL; PALM ACID; PALM KERNEL ACID; PENTASODIUM PENTETATE; PEPPERMINT OIL; PROPYLENE GLYCOL; SILVER OXIDE; SODIUM STEARATE; SHEA BUTTER; SODIUM LAURETH SULFATE; STEARIC ACID; SODIUM CHLORIDE; SODIUM PALMATE; SODIUM PALM KERNELATE; SORBITOL; TITANIUM DIOXIDE; ETIDRONATE TETRASODIUM; WATER; WHITE WAX; ZINC OXIDE

Drug Facts

Active Ingredients

Allantoin 0.5%, Lidocaine HCL 0.5%

Purpose

Allantoin - Skin Protectant

Lidocaine HCL - Topical Anesthetic

Uses

For temporary protection and relief of pain and itching associated with minor skin irritations, rashes, eczema and/or insect bites.

Warnings

For external use only. Avoid contact with eyes. Do not apply to open wounds
or damaged skin. If symptoms persist for more than seven days, discontinue use and
consult physician.
If pregnant or breast feeding, contact physician prior to use.

Keep out of reach of children.

If swallowed, consult physician.

Directions

Ointment: Apply directly to affected area. Do not use more than four
times per day. Store at room temperature. May stain fabrics.

Cleansing Bar: Wash affected area daily.

Inactive Ingredients

Ointment: beeswax (organic), bentonite (volcanic clay), eucalyptus citriodora oil, jojoba seed oil, magnesium oxide, peppermint oil, silver oxide, zinc oxide.

Cleansing Bar: beeswax, bentonite clay, coconut oil, eucalyptus oil, glycerin, jojoba seed oil, lauric acid, lavender oil, magnesium oxide, olive oil, palm acid, palm kernel acid, pentasodium pentetate, peppermint oil, propylene glycol, purified water, silver oxide, sodium stearate, sorbitol, shea butter, sodium laureth sulphate (SLES), stearic acid, sodium chloride, sodium palmate, sodium palm kernelate, sorbitol, titanium dioxide, tetrasodium etidronate, zinc oxide.

PRINCIPAL DISPLAY PANEL - BOX

Itch, Rash & Pain

- Penetrating Pain and Intense Itching
- Eczema, Dermatitis, Insect Bites
- Rashes and Red Irritated Skin

All Natural

terrasil

ITCH, RASH & PAIN RELIEF OINTMENT

Plus Medicated Cleansing Bar

FAST & EFFECTIVE

itch and pain relief

THE END OF SUFFERING SKIN

Healing and Relief Since 2004